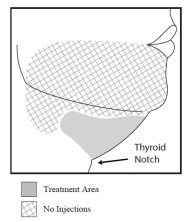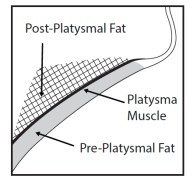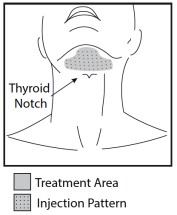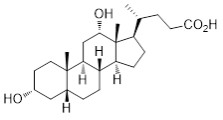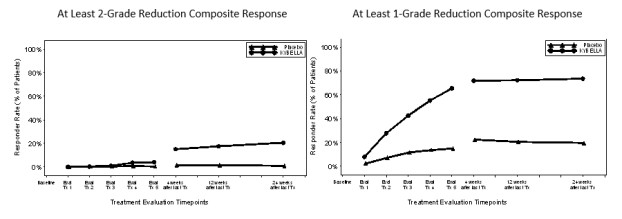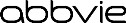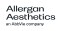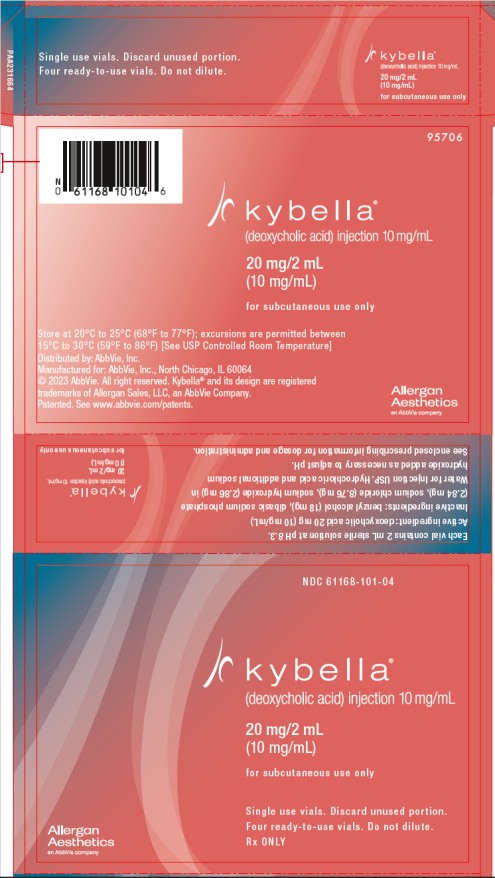 DRUG LABEL: KYBELLA
NDC: 61168-101 | Form: INJECTION, SOLUTION
Manufacturer: Kythera Biopharmaceuticals Inc.
Category: prescription | Type: HUMAN PRESCRIPTION DRUG LABEL
Date: 20241030

ACTIVE INGREDIENTS: DEOXYCHOLIC ACID 20 mg/2 mL
INACTIVE INGREDIENTS: BENZYL ALCOHOL 18 mg/2 mL; SODIUM PHOSPHATE, DIBASIC 2.84 mg/2 mL; SODIUM CHLORIDE 8.76 mg/2 mL; SODIUM HYDROXIDE 2.86 mg/2 mL; WATER; HYDROCHLORIC ACID

HIGHLIGHTS OF PRESCRIBING INFORMATION

These highlights do not include all the information needed to use KYBELLA safely and effectively. See full prescribing information for KYBELLA.
KYBELLA® (deoxycholic acid) injection, for subcutaneous use
Initial U.S. Approval: 2015

1 INDICATIONS AND USAGE

KYBELLA is a cytolytic drug indicated for improvement in the appearance of moderate to severe convexity or fullness associated with submental fat in adults. (1)

Limitations of use

The safe and effective use of KYBELLA for the treatment of subcutaneous fat outside the submental region has not been established and is not recommended. (1)

2 DOSAGE AND ADMINISTRATION

- 0.2 mL injections spaced 1 cm apart until all sites in the planned treatment area have been injected. (2.1)
- Up to 50 injections or 10 mL may be injected in a single treatment. (2.1)
- Up to 6 single treatments may be administered at intervals no less than 1-month apart. (2.1)
- See General Considerations for Administration and Injection Technique before injection. (2.2, 2.3)

3 DOSAGE FORMS AND STRENGTHS

Injection: 10 mg/mL. (3)

4 CONTRAINDICATIONS

KYBELLA is contraindicated:

- In the presence of infection at the injection sites. (4)

5 WARNINGS AND PRECAUTIONS

- Marginal mandibular nerve (MMN) injury: Follow injection technique to avoid this injury. (2.3, 5.1)
- Dysphagia may occur with KYBELLA use. Use in patients with pre-existing dysphagia may exacerbate the condition. (5.2)
- Submental hematoma/bruising occurs frequently after KYBELLA administration. Use with caution in patients who are being treated with antiplatelet or anticoagulant therapy or have coagulation abnormalities. (5.3)
- Avoid injecting in proximity to vulnerable anatomic structures due to the increased risk of tissue damage and vascular injury. (2.3, 5.4)
- Injection site alopecia: Withhold subsequent treatments until resolution. (5.5)
- Injection site ulceration, necrosis, and infection: Do not administer to the affected area until complete resolution. (5.6)

6 ADVERSE REACTIONS

The most common adverse reactions (>20% of subjects) include injection site edema/swelling, hematoma, pain, numbness, erythema and induration. (6.1)

To report SUSPECTED ADVERSE REACTIONS, contact Allergan at 1-800-678-1605 or FDA at 1-800-FDA-1088 or www.fda.gov/medwatch.

FULL PRESCRIBING INFORMATION

1 INDICATIONS AND USAGE

KYBELLA® (deoxycholic acid) injection is indicated for improvement in the appearance of moderate to severe convexity or fullness associated with submental fat in adults.

Limitations of use

The safe and effective use of KYBELLA for the treatment of subcutaneous fat outside the submental region has not been established and is not recommended.

2 DOSAGE AND ADMINISTRATION

2.1 Dosage

KYBELLA injection is injected into subcutaneous fat tissue in the submental area using an area-adjusted dose of 2 mg/cm^2.

- A single treatment consists of up to a maximum of 50 injections, 0.2 mL each (up to a total of 10 mL), spaced 1 cm apart.
- Up to 6 single treatments may be administered at intervals no less than 1 month apart.

See General Considerations for Administration (2.2) and Injection Technique (2.3) before injection.

2.2 General Considerations for Administration

KYBELLA should be administered by a healthcare professional.

Screen patients for other potential causes of submental convexity/fullness (e.g., thyromegaly and cervical lymphadenopathy).

Give careful consideration to the use of KYBELLA in patients with excessive skin laxity, prominent platysmal bands or other conditions for which reduction of submental fat may result in an aesthetically undesirable outcome.

Use caution in patients who have had prior surgical or aesthetic treatment of the submental area. Changes in anatomy/landmarks or the presence of scar tissue may impact the ability to safely administer KYBELLA or to obtain the desired aesthetic result.

KYBELLA is clear, colorless and free of particulate matter. Visually inspect KYBELLA vials for particulate matter and/or discoloration, and discard the vial if the solution is discolored and/or contains particulate matter.

After use, discard any remaining solution in the vial.

2.3 Injection Technique

The safe and effective use of KYBELLA depends on the use of the correct number and locations for injections, proper needle placement, and administration techniques.

Healthcare professionals administering KYBELLA must understand the relevant submental anatomy and associated neuromuscular structures in the area involved and any alterations to the anatomy due to prior surgical or aesthetic procedures [see Warnings and Precautions (5)].

Avoid injections near the area of the marginal mandibular nerve

Needle placement with respect to the mandible is very important as it reduces the potential for injury to the marginal mandibular nerve, a motor branch of the facial nerve. Injury to the nerve presents as an asymmetrical smile due to paresis of lip depressor muscles [see Warnings and Precautions (5.1)].

To avoid injury to the marginal mandibular nerve:

- Do not inject above the inferior border of the mandible.
- Do not inject within a region defined by a 1-1.5 cm line below the inferior border (from the angle of the mandible to the mentum).
- Inject KYBELLA only within the target submental fat treatment area (see Figures 1 and 3).

Figure 1. Avoid the Marginal Mandibular Nerve Area

Avoid injection into the platysma

Prior to each treatment session, palpate the submental area to ensure sufficient submental fat and to identify subcutaneous fat between the dermis and platysma (pre-platysmal fat) within the target treatment area (Figure 2). The number of injections and the number of treatments should be tailored to the individual patient’s submental fat distribution and treatment goals.

Figure 2. Sagittal View of Platysma Area

Injecting into the treatment area

Use of ice/cold packs, topical and/or injectable local anesthesia (e.g., lidocaine) may enhance patient comfort.

Outline the planned treatment area with a surgical pen and apply a 1 cm injection grid to mark the injection sites (Figures 2 and 3).

Figure 3. Treatment Area and Injection Pattern

Do not inject KYBELLA outside the defined parameters [see Warnings and Precautions (5.1, 5.4, 5.6)].

- Using a large bore needle, draw 1 mL of KYBELLA into a sterile 1 mL syringe and expel any air bubbles in the syringe barrel.
- Have the patient tense the platysma. Pinch the submental fat and, using a 30 gauge (or smaller) 0.5 inch needle, inject 0.2 mL of KYBELLA into the pre-platysmal fat (see Figure 2) next to each of the marked injection sites by advancing the needle perpendicular to the skin.
- Injections that are too superficial (into the dermis) may result in skin ulceration and necrosis. Do not withdraw the needle from the subcutaneous fat during injection as this could increase the risk of intradermal exposure and potential skin ulceration and necrosis.
- Avoid injecting into the post-platysmal fat by injecting KYBELLA into fat tissue at the depth of approximately mid-way into the subcutaneous fat layer (Figure 2).
- If at any time resistance is met as the needle is inserted, indicating the possibility of contact with fascial or nonfat tissue, the needle must be withdrawn to an appropriate depth before the injection is administered.
- Avoid injecting into other tissues such as the muscle, salivary glands, lymph nodes; and artery or vein.
- Upon needle withdrawal, pressure may be applied to each injection site as necessary to minimize bleeding; an adhesive dressing may be applied.

3 DOSAGE FORMS AND STRENGTHS

Injection: 10 mg/mL.

KYBELLA (deoxycholic acid) injection is a clear, colorless, sterile solution supplied in 2 mL vials intended for single patient use. Each milliliter of the solution contains 10 mg of deoxycholic acid.

4 CONTRAINDICATIONS

KYBELLA injection is contraindicated in the presence of infection at the injection sites.

5 WARNINGS AND PRECAUTIONS

5.1 Marginal mandibular nerve injury

Cases of marginal mandibular nerve injury, manifested as an asymmetric smile or facial muscle weakness (paresis), were reported during clinical trials. To avoid the potential for nerve injury, KYBELLA injection should not be injected into or in close proximity to the marginal mandibular branch of the facial nerve. All marginal mandibular nerve injuries reported from the trials resolved spontaneously (range 1-298 days, median 44 days).

5.2 Dysphagia

Difficulty swallowing (dysphagia) occurred in clinical trials in the setting of administration site reactions, e.g., pain, swelling, and induration of the submental area. Cases of dysphagia spontaneously resolved (range 1-81 days, median 3 days).

Subjects with current or prior history of dysphagia were excluded from clinical trials. Avoid use of KYBELLA in these patients as current or prior history of dysphagia may exacerbate the condition.

5.3 Injection site hematoma/bruising

In clinical trials, 72% of subjects treated with KYBELLA experienced injection site hematoma/bruising [see Adverse Reactions (6.1)].

KYBELLA should be used with caution in patients with bleeding abnormalities or who are currently being treated with antiplatelet or anticoagulant therapy as excessive bleeding or bruising in the treatment area may occur.

5.4 Risk of injecting in proximity to vulnerable anatomic structures

To avoid potential tissue damage, KYBELLA should not be injected into or in close proximity (1-1.5 cm) to salivary glands, lymph nodes and muscles.

Care should be taken to avoid inadvertent injection directly into an artery or a vein as it can result in vascular injury.

5.5 Injection site alopecia

Cases of injection site alopecia have been reported with the administration of KYBELLA. The onset and duration of this adverse reaction may vary among individuals and may persist. Consider withholding subsequent treatments until resolution of the adverse reaction.

5.6 Injection site ulceration, necrosis, and infection

Injections that are too superficial (into the dermis) may result in skin ulceration and necrosis [see Injection Technique (2.3)]. Cases of injection site ulceration, necrosis, and infection have been reported with the administration of KYBELLA. Some cases of injection site infection have included cellulitis and abscess requiring intravenous antibiotic treatment and incision and drainage. Do not administer KYBELLA into the affected area until complete resolution of the adverse reaction.

6 ADVERSE REACTIONS

6.1 Clinical Trials Experience

Because clinical trials are conducted under widely varying conditions, the adverse reaction rates observed in the clinical trials of a drug cannot be directly compared to rates in the clinical trials of another drug and may not reflect the rates observed in practice.

In two double-blind, placebo-controlled clinical trials 513 subjects were treated with KYBELLA injection and 506 subjects were treated with placebo. The population was 19-65 years old, 85% were women, 87% Caucasian, 8% African American. At baseline the population had a mean BMI of 29 kg/m^2, moderate to severe submental convexity (graded as 2 or 3 on a 0 to 4 scale) and without excessive skin laxity. Subjects received up to 6 treatments at least 1 month apart and were followed for up to 6 months after the last received treatment.

The most commonly reported adverse reactions are listed below (Table 1).

Table 1. Adverse Reactions in the Pooled Trials 1 and 2a
Adverse reactions | KYBELLA (N=513) n (%) | Placebo (N=506) n (%)
Injection site reactions | 492 (96%) | 411 (81%)
edema/swelling | 448 (87%) | 218 (43%)
hematoma/bruising | 368 (72%) | 353 (70%)
pain | 356 (70%) | 160 (32%)
numbness | 341 (66%) | 29 (6%)
erythema | 136 (27%) | 91 (18%)
induration | 120 (23%) | 13 (3%)
paresthesia | 70 (14%) | 20 (4%)
nodule | 68 (13%) | 14 (3%)
pruritus | 64 (12%) | 30 (6%)
skin tightness | 24 (5%) | 6 (1%)
site warmth | 22 (4%) | 8 (2%)
nerve injury b | 20 (4 %) | 1 (<1%)
Headache | 41 (8%) | 20 (4%)
Oropharyngeal pain | 15 (3%) | 7 (1%)
Hypertension | 13 (3%) | 7 (1%)
Nausea | 12 (2%) | 3 (1%)
Dysphagia | 10 (2%) | 1 (<1%)

a Adverse reactions that occurred in ≥ 2% KYBELLA treated subjects and at greater incidence than placebo
b Marginal mandibular nerve paresis

Other adverse reactions associated with the use of KYBELLA include: injection site hemorrhage, injection site discoloration, pre-syncope/syncope, lymphadenopathy, injection site urticaria, and neck pain.

Adverse reactions that lasted more than 30 days and occurred in more than 10% of subjects were injection site numbness (42%), injection site edema/swelling (20%), injection site pain (16%), and injection site induration (13%).

6.2 Postmarketing Experience

The following adverse reactions have been identified during post-approval use of KYBELLA.

Because these reactions are reported voluntarily from a population of uncertain size, it is not always possible to reliably estimate their frequency or establish a causal relationship to KYBELLA exposure.

Administration site conditions: injection site ulceration, necrosis, infection, alopecia, scarring, and mass.

Immune System Disorders: Hypersensitivity reactions including rash, urticaria, and itching.

Nervous System Disorders: Oral hypoaesthesia and oral paraesthesia.

Procedural Complications: Vascular injury due to inadvertent intravascular injection.

8 USE IN SPECIFIC POPULATIONS

8.1 Pregnancy

Risk Summary

There are no adequate and well-controlled studies of KYBELLA injection in pregnant women to inform the drug-associated risk. In animal reproduction studies, no fetal harm was observed with the subcutaneous administration of deoxycholic acid to rats during organogenesis at doses up to 5 times the maximum recommended human dose (MRHD) of 100 mg [see Data].

The background risk of major birth defects and miscarriage for the indicated population is unknown. However, the background risk of major birth defects in the U.S. general population is 2-4% and of miscarriage is 15-20% of clinically recognized pregnancies.

Data

Animal Data

Embryofetal development studies have been performed in rats and rabbits using subcutaneous doses of deoxycholic acid administered during the period of organogenesis. For the basis of comparing animal to human doses, the MRHD is 1.7 mg/kg (100 mg/60 kg). No evidence of fetal harm was observed in rats at up to the highest dose tested (50 mg/kg) which is 5-fold higher than the MRHD of KYBELLA based on a mg/m^2 comparison. However, missing intermediate lung lobe was noted in rabbits at all dose levels tested including the lowest dose (10 mg/kg) which is 2-fold higher than the MRHD of KYBELLA based on a mg/m^2 comparison. These effects may be related to maternal toxicity, which was also seen at all dose levels tested.

8.2 Lactation

Risk Summary

There is no information available on the presence of synthetic deoxycholic acid in human milk, the effects of the drug on the breastfed infant or the effects of the drug on milk production. The developmental and health benefits of breastfeeding should be considered along with the mother's clinical need for KYBELLA and any potential adverse effects on the breastfed child from KYBELLA or from the underlying maternal condition.

8.4 Pediatric Use

Safety and effectiveness in patients below the age of 18 years have not been established and KYBELLA is not intended for use in children or adolescents.

8.5 Geriatric Use

The clinical trials of KYBELLA did not include sufficient numbers of subjects aged 65 and over to determine whether they respond differently from younger subjects. Other reported clinical experience has not identified differences in responses between the elderly and younger subjects. In general, dose selection for an elderly patient should be cautious, usually starting at the low end of the dosing range, reflecting the greater frequency of decreased hepatic, renal, or cardiac function, and of concomitant disease or other drug therapy.

11 DESCRIPTION

KYBELLA (deoxycholic acid) injection, 10 mg/mL is a clear colorless, sterile solution for subcutaneous use. It contains a cytolytic agent, deoxycholic acid, as the active ingredient. The chemical name of deoxycholic acid is 3α,12α-dihydroxy-5β-cholan-24-oic acid, and its molecular formula is C24H40O4, and its molecular weight is 392.57 g/mol. The chemical structure of deoxycholic acid is:

Each 2 mL vial of KYBELLA injection contains 20 mg synthetic deoxycholic acid as the active ingredient and the following inactive ingredients: benzyl alcohol (18 mg), dibasic sodium phosphate (2.84 mg), sodium chloride (8.76 mg), sodium hydroxide (2.86 mg) in water for injection, USP. Hydrochloric acid and additional sodium hydroxide are added as necessary to adjust the formulation to pH 8.3. Each vial is for single patient use.

12 CLINICAL PHARMACOLOGY

12.1 Mechanism of Action

KYBELLA injection is a cytolytic drug, which when injected into tissue physically destroys the cell membrane causing lysis.

12.2 Pharmacodynamics

Cardiac Electrophysiology

At therapeutic doses, KYBELLA does not prolong the QTc interval.

12.3 Pharmacokinetics

Endogenous deoxycholic acid plasma levels are highly variable within and between individuals; most of this natural bile component is sequestered in the enterohepatic circulation loop.

Absorption and Distribution

Deoxycholic acid from KYBELLA is rapidly absorbed following subcutaneous injection. After dosing with the maximum recommended single treatment dose with KYBELLA (100 mg), maximum plasma concentrations (mean Cmax) were observed with a median Tmax of 18 minutes after injection. The mean (±SD) Cmax value was 1024 ± 304 ng/mL and was 3.2-fold higher than average Cmax values observed during a 24-hour baseline endogenous period in the absence of KYBELLA. After maximum recommended single treatment dose (100 mg), mean (±SD) deoxycholic acid exposure (AUC0-24) was 7896 ± 2269 ng.hr/mL and was 1.6-fold higher over endogenous exposure. Post-treatment deoxycholic acid plasma levels returned to the endogenous range within 24 hours. No accumulation is expected with the proposed treatment frequency.

Deoxycholic acid is extensively bound to proteins in plasma (98%).

Metabolism and Excretion

Endogenous deoxycholic acid is a product of cholesterol metabolism and is excreted intact in feces. Deoxycholic acid is not metabolized to any significant extent under normal conditions. Deoxycholic acid from KYBELLA joins the endogenous bile acid pool in the enterohepatic circulation and is excreted along with the endogenous deoxycholic acid.

In Vitro Assessment of Drug Interactions

Results from in vitro studies indicate that deoxycholic acid does not inhibit or induce human cytochrome P450 (CYP) enzymes at clinically relevant concentrations. Deoxycholic acid does not inhibit the following transporters: P-gp, BCRP, MRP4, MRP2, OATP1B1, OATP2B1, OATP1B3, OCT1, OCT2, OAT1, OAT3, NTCP, and ASBT.

Specific Populations

Hepatic Impairment

KYBELLA has not been studied in subjects with hepatic impairment. Considering the intermittent dose frequency, the small dose administered that represents approximately 3% of the total bile acid pool, and the highly variable endogenous deoxycholic acid levels, the pharmacokinetics of deoxycholic acid following KYBELLA injection is unlikely to be influenced by hepatic impairment.

Pharmacokinetic Effects of Gender

Deoxycholic acid pharmacokinetics were not influenced by gender.

13 NONCLINICAL TOXICOLOGY

13.1 Carcinogenesis, Mutagenesis, Impairment of Fertility

Long-term studies in animals have not been performed to evaluate the carcinogenic potential of KYBELLA injection.

KYBELLA was negative in a battery of in vitro (Ames test and chromosomal aberration assay in human lymphocytes) and in vivo (rat erythrocyte micronucleus assay) genetic toxicology assays.

No effects on fertility were observed in male and female rats administered deoxycholic acid at subcutaneous doses up to 50 mg/kg (5 times the MRHD based on a mg/m^2 comparison) once weekly prior to and during the mating period and through gestation day 7 in female rats.

14 CLINICAL STUDIES

Two randomized, multi-center, double-blind, placebo-controlled trials of identical design were conducted to evaluate KYBELLA injection for use in improvement in the appearance of convexity or fullness associated with submental fat. The trials enrolled healthy adults (ages 19 to 65, BMI ≤ 40 kg/m^2) with moderate or severe convexity or fullness associated with submental fat (i.e., grade 2 or 3 on 5-point grading scales, where 0 = none and 4 = extreme), as judged by both clinician and subject ratings. Subjects received up to 6 treatments with KYBELLA (N=514, combined trials) or placebo (N=508, combined trials) at no less than 1 month intervals. Use of ice/cold packs, topical and/or injectable local anesthesia was allowed during the clinical trials. Injection volume was 0.2 mL per injection site, spaced 1 cm apart into the submental fat tissue, which is also expressed in dose per area as 2 mg/cm^2. For each treatment session a maximum of 100 mg (10 mL) was permitted over the entire treatment area. Subjects were administered an average of 6.4 mL at the first treatment session, and subjects who received all six treatments were administered an average of 4.4 mL at the sixth treatment session. Fifty-nine percent of subjects received all six treatments.

In these trials, the mean age was 49 years and the mean BMI was 29 kg/m^2. Most of the subjects were women (85%) and Caucasian (87%). At baseline, 51% of the subjects had a clinician-rated submental fat severity rating of moderate and 49% had a severe submental fat rating.

The co-primary efficacy assessments were based on at least 2-grade and at least 1-grade improvements in submental convexity or fullness on the composite of clinician-reported and patient-reported ratings of submental fat 12 weeks after final treatment. Additionally, changes in submental fat volume were evaluated in a subset of subjects (N=449, combined trials) using magnetic resonance imaging (MRI). Visual and emotional impacts of submental fat (happy, bothered, self-conscious, embarrassed, looking older or overweight) were also evaluated using a 6-question survey, with each question rated from 0 (not at all) to 10 (extremely/very much).

Reductions in submental fat volume were observed more frequently in the KYBELLA group compared to the placebo group as measured by the composite clinician and patient ratings (Table 2). The composite response rates by visit are presented in Figure 4.

Table 2. ≥ 2-Grade and ≥ 1-Grade Composite Clinician and Patient Response 12 Weeks After Final Treatment
 | Trial 1 |  | Trial 2
Endpoint | KYBELLA (N=256) | Placebo (N=250) | KYBELLA (N=258) | Placebo (N=258)
2-Grade Composite Response a | 13.4% | <0.1% | 18.6% | 3.0%
1-Grade Composite Response b | 70.0% | 18.6% | 66.5% | 22.2%

a At least 2 grade reduction on both the clinician-reported and patient-reported ratings of submental fat
b At least 1 grade reduction on both the clinician-reported and patient-reported ratings of submental fat

Figure 4. ≥ 2-Grade and ≥ 1-Grade Composite Clinician and Patient Response

Note: Subjects were followed up 4, 12 and 24 weeks after the last treatment. Forty-one percent of subjects received fewer than 6 treatments and entered the post-treatment period earlier than Week 24.

A greater proportion of KYBELLA-treated subjects had at least a 10% reduction in submental fat volume as compared to placebo-treated subjects when evaluated by MRI (43% vs 5%, respectively).

The overall patient-reported satisfaction and self-perceived visual attributes showed greater improvement in the KYBELLA group than in the placebo group.

16 HOW SUPPLIED/STORAGE AND HANDLING

KYBELLA (deoxycholic acid) injection, 10 mg/mL is a clear, colorless, sterile solution supplied in 2 mL, single patient use vials in the following dispensing pack:

4 vials, NDC 61168-101-04

Store at 20°C to 25°C (68°F to 77°F); excursions are permitted between 15°C to 30°C (59°F to 86°F) [See USP Controlled Room Temperature].

KYBELLA has a unique hologram on the vial label. If you do not see a hologram, do not use the product and call 1-800-678-1605.

Each vial is for a single patient use. Do not dilute or mix KYBELLA with other compounds. Discard unused portion.

17 PATIENT COUNSELING INFORMATION

Advise the patient to read the FDA-approved patient labeling (Patient Information).

Advise patients to contact their healthcare providers if patients begin to develop signs of marginal mandibular nerve paresis (e.g., asymmetric smile, facial muscle weakness), difficulty swallowing, or worsening of existing symptoms.

Advise patients to contact their healthcare providers for development of erythema, pain, open sore(s) or drainage from the treatment area.

Distributed by: AbbVie Inc.

Manufactured for:
AbbVie Inc.
North Chicago, IL 60064
© 2024 AbbVie. All rights reserved.
KYBELLA® and its design are registered trademarks of Allergan Sales, LLC, an AbbVie company.

Patented. See www.abbvie.com/patents

v4.0USPI0101

Patient Information
KYBELLA® (kye be lah)
(deoxycholic acid)
injection

What is KYBELLA?
KYBELLA is a prescription medicine used in adults to improve the appearance and profile of moderate to severe fat below the chin (submental fat), also called “double chin.”
It is not known if KYBELLA is safe and effective for the treatment of fat outside of the submental area.
It is not known if KYBELLA is safe and effective in children under 18 years of age.

Do not receive KYBELLA if you have an infection in the treatment area.

Before receiving KYBELLA, tell your healthcare provider about all of your medical conditions, including if you:

- have had or plan to have surgery on your face, neck, or chin
- have had cosmetic treatments on your face, neck, or chin
- have had or have medical conditions in or near the neck area
- have had or have trouble swallowing
- have bleeding problems
- are pregnant or plan to become pregnant. It is not known if KYBELLA will harm your unborn baby.
- are breastfeeding or plan to breastfeed. It is not known if KYBELLA passes into your breast milk.

Tell your healthcare provider about all the medicines you take, including prescription and over-the-counter medicines, vitamins, and herbal supplements. Especially tell your healthcare provider if you take a medicine that prevents the clotting of your blood (antiplatelet or anticoagulant medicine).

How will I receive KYBELLA?

- KYBELLA is injected into the fat under your chin (up to 50 injections under your skin) by your healthcare provider.
- KYBELLA injections may be given at least 1 month apart. You and your healthcare provider will decide how many treatments you need.

What are the possible side effects of KYBELLA?
KYBELLA can cause serious side effects, including:

- Nerve injury in the jaw that can cause an uneven smile or facial muscle weakness.
- Trouble swallowing.
- Injection site problems including:
  - a collection of blood under the skin (hematoma) or bruising
  - damage to an artery or vein if KYBELLA is inadvertently injected into it
  - hair loss
  - open sores (ulcers)
  - damage and tissue cell-death (necrosis) around the injection site
  - infection

Call your healthcare provider if you:

- begin to develop weakness in the muscles of your face, or your smile becomes uneven
- you have difficulty swallowing, or if any of the symptoms that you already have get worse
- develop redness, pain, open sores, or drainage at or from the treatment area

The most common side effects of KYBELLA include:

● swelling

● redness

● pain

● areas of hardness in the treatment area

● numbness

These are not all of the possible side effects of KYBELLA.
Call your doctor for medical advice about side effects. You may report side effects to FDA at 1-800-FDA-1088.

General information about the safe and effective use of KYBELLA.
Medicines are sometimes prescribed for purposes other than those listed in a Patient Information leaflet. If you would like more information, talk to your healthcare provider. You can ask your pharmacist or healthcare provider for more information about KYBELLA that is written for health professionals.

What are the ingredients in KYBELLA?
Active ingredient: deoxycholic acid
Inactive ingredients: benzyl alcohol, dibasic sodium phosphate, hydrochloric acid, sodium chloride, sodium hydroxide and water for injection, USP.

Distributed by: AbbVie Inc.
Manufactured for:
AbbVie Inc.
North Chicago, IL 60064
© 2024 AbbVie. All rights reserved.
KYBELLA® and its design are registered trademarks of Allergan Sales, LLC, an AbbVie
company.
Patented. See www.abbvie.com/patents
For more information about KYBELLA go to www.mykybella.com.

This Patient Information has been approved by the U.S. Food and Drug Administration. Revised: 10/2024

v4.0PPI0101

PACKAGE LABEL

Principal Display Panel

NDC: 61168-101-04
kybella®
(deoxycholic acid) injection 10 mg/mL
20 mg/2 mL
(10 mg/mL)
for subcutaneous use only

Single use vials. Discard unused portion.

Four ready-to-use vials. Do not dilute.

Rx ONLY